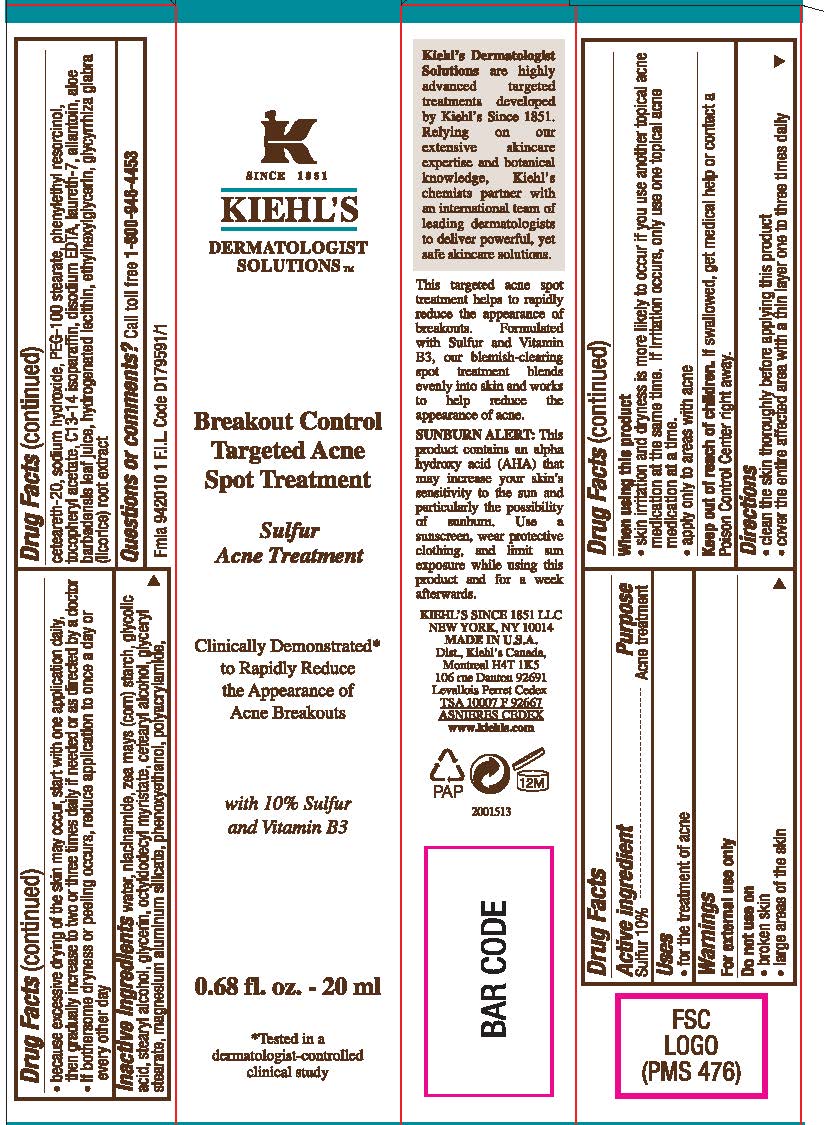 DRUG LABEL: Kiehls Since 1851 Dermatologist Solutions Breakout Control Targeted Acne Spot Treatment
NDC: 49967-895 | Form: LOTION
Manufacturer: L'Oreal USA Products Inc
Category: otc | Type: HUMAN OTC DRUG LABEL
Date: 20231230

ACTIVE INGREDIENTS: SULFUR 100 mg/1 mL
INACTIVE INGREDIENTS: WATER; NIACINAMIDE; GLYCOLIC ACID; STEARYL ALCOHOL; GLYCERIN; PHENOXYETHANOL; SODIUM HYDROXIDE; PEG-100 STEARATE; PHENYLETHYL RESORCINOL; ALLANTOIN; ETHYLHEXYLGLYCERIN

Drug Facts

Active ingredient

Sulfur 10%

Purpose

Acne treatment

Use

for the treatment of acne

Warnings

For external use only

Do not use on

- broken skin
- large areas of the skin

When using this product

- skin irritation and dryness is more likely to occur if you use another topical acne medication at the same time. If irritation occurs, only use one topical acne medication at a time.
- apply only to areas with acne

Keep out of reach of children.

If swallowed, get medical help or contact a Poison Control Center right away.

Directions

- clean the skin thoroughly before applying this product
- cover the entire affected area with a thin layer one to three times daily
- because excessive drying of the skin may occur, start with one application daily, then gradually increase to two or three times daily if needed or as directed by a doctor
- if bothersome dryness or peeling occurs, reduce application to once a day or every other day

Inactive ingredient

water, niacinamide, zea mays (corn) starch, glycolic acid, stearyl alcohol, glycerin, octyldodecyl myristate, cetearyl alcohol, glyceryl stearate, magnesium aluminum silicate, phenoxyethanol, polyacrylamide, ceteareth-20, sodium hydroxide, PEG-100 stearate, phenylethyl resorcinol, tocopheryl acetate, C13-14 isoparaffin, disodium EDTA, laureth-7, allantoin, aloe barbadensis leaf juice, hydrogenated lecithin, ethylhexylglycerin, glycyrrhiza glabra (licorice) root extract

Questions or comments?

Call toll free 1-800-946-4453